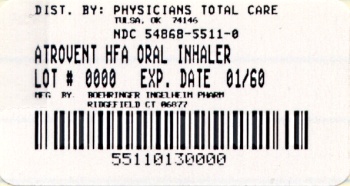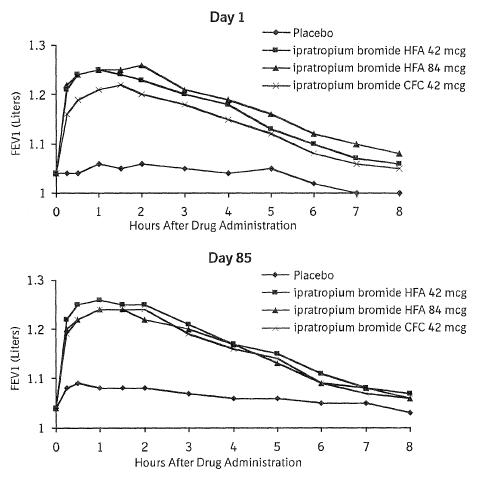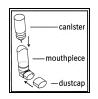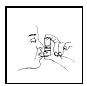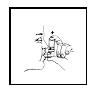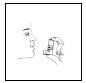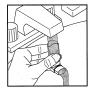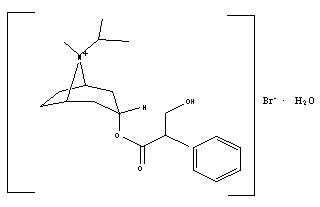 DRUG LABEL: AtroventHFA
NDC: 54868-5511 | Form: AEROSOL, METERED
Manufacturer: Physicians Total Care, Inc.
Category: prescription | Type: HUMAN PRESCRIPTION DRUG LABEL
Date: 20100728

ACTIVE INGREDIENTS: IPRATROPIUM BROMIDE 17 ug/1 1
INACTIVE INGREDIENTS: NORFLURANE; WATER; ALCOHOL; ANHYDROUS CITRIC ACID

Atrovent® HFA
(ipratropium bromide HFA)
Inhalation Aerosol

ATTENTION PHARMACIST: Detach "Patient's Instructions for Use" from package insert and dispense with the product.

For Oral Inhalation Only

Prescribing Information

DESCRIPTION

The active ingredient in ATROVENT HFA Inhalation Aerosol is ipratropium bromide (as the monohydrate). It is an anticholinergic bronchodilator chemically described as 8-azoniabicyclo[3.2.1]octane, 3-(3-hydroxy-1-oxo-2-phenylpropoxy)-8-methyl-8-(1-methylethyl)-,bromide monohydrate, (3-endo, 8-syn)-: a synthetic quaternary ammonium compound, chemically related to atropine. The structural formula for ipratropium bromide is:

C20H30BrNO3•H2O ipratropium bromide Mol. Wt. 430.4

Ipratropium bromide is a white to off-white crystalline substance, freely soluble in water and methanol, sparingly soluble in ethanol, and insoluble in lipophilic solvents such as ether, chloroform, and fluorocarbons.

ATROVENT HFA Inhalation Aerosol is a pressurized metered-dose aerosol unit for oral inhalation that contains a solution of ipratropium bromide. The 200 inhalation unit has a net weight of 12.9 grams. After priming, each actuation of the inhaler delivers 21 mcg of ipratropium bromide from the valve in 56 mg of solution and delivers 17 mcg of ipratropium bromide from the mouthpiece. The actual amount of drug delivered to the lung may depend on patient factors, such as the coordination between the actuation of the device and inspiration through the delivery system. The excipients are HFA-134a (1,1,1,2-tetrafluoroethane) as propellant, sterile water, dehydrated alcohol, and anhydrous citric acid. This product does not contain chlorofluorocarbons (CFCs) as propellants.

Atrovent® HFA (ipratropium bromide HFA) Inhalation Aerosol should be primed before using for the first time by releasing 2 test sprays into the air away from the face. In cases where the inhaler has not been used for more than 3 days, prime the inhaler again by releasing 2 test sprays into the air away from the face.

CLINICAL PHARMACOLOGY

Mechanism of Action

Ipratropium bromide is an anticholinergic (parasympatholytic) agent which, based on animal studies, appears to inhibit vagally-mediated reflexes by antagonizing the action of acetylcholine, the transmitter agent released at the neuromuscular junctions in the lung. Anticholinergics prevent the increases in intracellular concentration of Ca++ which is caused by interaction of acetylcholine with the muscarinic receptors on bronchial smooth muscle.

Pharmacodynamic Properties

Controlled clinical studies have demonstrated that Atrovent® (ipratropium bromide) Inhalation Aerosol CFC does not alter either mucociliary clearance or the volume or viscosity of respiratory secretions.

Pharmacokinetics

Most of an administered dose is swallowed as shown by fecal excretion studies. Ipratropium bromide is a quaternary amine. It is not readily absorbed into the systemic circulation either from the surface of the lung or from the gastrointestinal tract as confirmed by blood level and renal excretion studies.

Autoradiographic studies in rats have shown that ipratropium bromide does not penetrate the blood-brain barrier. The half-life of elimination is about 2 hours after inhalation or intravenous administration. Ipratropium bromide is minimally bound (0 to 9% in vitro) to plasma albumin and α1-acid glycoprotein. It is partially metabolized to inactive ester hydrolysis products. Following intravenous administration, approximately one-half of the dose is excreted unchanged in the urine.

A pharmacokinetic study with 29 chronic obstructive pulmonary disease (COPD) patients (48-79 years of age) demonstrated that mean peak plasma ipratropium concentrations of 59±20 pg/mL were obtained following a single administration of 4 inhalations of ATROVENT HFA Inhalation Aerosol (84 mcg). Plasma ipratropium concentrations rapidly declined to 24±15 pg/mL by six hours. When these patients were administered 4 inhalations QID (16 inhalations/day=336 mcg) for one week, the mean peak plasma ipratropium concentration increased to 82±39 pg/mL with a trough (6 hour) concentration of 28±12 pg/mL at steady state.

Special Populations

Geriatric Patients

In the pharmacokinetic study with 29 COPD patients, a subset of 14 patients were > 65 years of age. Mean peak plasma ipratropium concentrations of 56±24 pg/mL were obtained following a single administration of 4 inhalations (21 mcg/puff) of Atrovent® HFA (ipratropium bromide HFA) Inhalation Aerosol (84 mcg). When these 14 patients were administered 4 inhalations QID (16 inhalations/day) for one week, the mean peak plasma ipratropium concentration only increased to 84±50 pg/mL indicating that the pharmacokinetic behavior of ipratropium bromide in the geriatric population is consistent with younger patients.

Renally Impaired Patients

The pharmacokinetics of ATROVENT HFA Inhalation Aerosol have not been studied in patients with renal insufficiency.

Hepatically Impaired Patients

The pharmacokinetics of ATROVENT HFA Inhalation Aerosol have not been studied in patients with hepatic insufficiency.

CLINICAL STUDIES

Conclusions regarding the efficacy of ATROVENT HFA Inhalation Aerosol were derived from two randomized, double-blind, controlled clinical studies. These studies enrolled males and females ages 40 years and older, with a history of COPD, a smoking history of > 10 pack- years, an FEV1 < 65% and an FEV1/FVC < 70%.

One of the studies was a 12-week randomized, double-blind active and placebo controlled study in which 505 of the 507 randomized COPD patients were evaluated for the safety and efficacy of 42 mcg (n=124) and 84 mcg (n=126) ATROVENT HFA Inhalation Aerosol in comparison to 42 mcg (n=127) Atrovent® (ipratropium bromide) Inhalation Aerosol CFC and their respective placebos (HFA n=62, CFC n=66). Data for both placebo HFA and placebo CFC were combined in the evaluation.

Serial FEV1 (shown in Figure 1, below, as means adjusted for center and baseline effects on test day 1 and test day 85 (primary endpoint)) demonstrated that 1 dose (2 inhalations/21 mcg each) of ATROVENT HFA Inhalation Aerosol produced significantly greater improvement in pulmonary function than placebo. During the six hours immediately post-dose on day 1, the average hourly improvement in adjusted mean FEV1 was 0.148 liters for ATROVENT HFA Inhalation Aerosol (42 mcg) and 0.013 liters for placebo. The mean peak improvement in FEV1, relative to baseline, was 0.295 liters, compared to 0.138 liters for placebo. During the six hours immediately post-dose on day 85, the average hourly improvement in adjusted mean FEV1 was 0.141 liters for ATROVENT HFA Inhalation Aerosol (42 mcg) and 0.014 liters for placebo. The mean peak improvement in FEV1, relative to baseline, was 0.295 liters, compared to 0.140 liters for placebo.

ATROVENT HFA Inhalation Aerosol (42 mcg) was shown to be clinically comparable to ATROVENT Inhalation Aerosol CFC (42 mcg).

Figure 1 Day 1 and Day 85 (Primary Endpoint) Results

In this study, both Atrovent® HFA (ipratropium bromide HFA) Inhalation Aerosol and Atrovent® (ipratropium bromide) Inhalation Aerosol CFC formulations were equally effective in patients over 65 years of age and under 65 years of age.

The median time to improvement in pulmonary function (FEV1 increase of 15% or more) was within approximately 15 minutes, reached a peak in 1-2 hours, and persisted for 2 to 4 hours in the majority of the patients. Improvements in Forced Vital Capacity (FVC) were also demonstrated.

The other study was a 12-week, randomized, double-blind, active-controlled clinical study in 174 adults with COPD, in which ATROVENT HFA Inhalation Aerosol 42 mcg (n=118) was compared to ATROVENT Inhalation Aerosol CFC 42 mcg (n=56). Safety and efficacy of HFA and CFC formulations were shown to be comparable.

The bronchodilatory efficacy and comparability of Atrovent® HFA (ipratropium bromide HFA) Inhalation Aerosol vs. Atrovent® (ipratropium bromide) Inhalation Aerosol CFC were also studied in a one-year open-label safety and efficacy study in 456 COPD patients. The safety and efficacy of HFA and CFC formulations were shown to be comparable.

INDICATIONS AND USAGE

ATROVENT HFA Inhalation Aerosol is indicated as a bronchodilator for maintenance treatment of bronchospasm associated with chronic obstructive pulmonary disease, including chronic bronchitis and emphysema.

CONTRAINDICATIONS

ATROVENT HFA Inhalation Aerosol is contraindicated in patients with a history of hypersensitivity to ipratropium bromide or other ATROVENT HFA Inhalation Aerosol components. ATROVENT HFA Inhalation Aerosol is also contraindicated in patients who are hypersensitive to atropine or its derivatives.

WARNINGS

ATROVENT HFA Inhalation Aerosol is a bronchodilator for the maintenance treatment of bronchospasm associated with COPD and is not indicated for the initial treatment of acute episodes of bronchospasm where rescue therapy is required for rapid response.

Immediate hypersensitivity reactions may occur after administration of ipratropium bromide, as demonstrated by urticaria, angioedema, rash, bronchospasm, anaphylaxis, and oropharyngeal edema. If such a reaction occurs, therapy with ATROVENT HFA should be stopped at once and alternative treatment should be considered.

Inhaled medicines, including ATROVENT HFA Inhalation Aerosol, may cause paradoxical bronchospasm. If this occurs, treatment with ATROVENT HFA Inhalation Aerosol should be stopped and other treatments considered.

PRECAUTIONS

General

ATROVENT HFA Inhalation Aerosol should be used with caution in patients with narrow-angle glaucoma, prostatic hyperplasia or bladder-neck obstruction.

Information for Patients

Appropriate and safe use of ATROVENT HFA Inhalation Aerosol includes providing the patient with the information listed below and an understanding of the way it should be administered (see Patient's Instructions for Use).

Patients should be advised that ATROVENT HFA Inhalation Aerosol is a bronchodilator for the maintenance treatment of bronchospasm associated with COPD and is not indicated for the initial treatment of acute episodes of bronchospasm where rescue therapy is required for rapid response.

Patients should be cautioned to avoid spraying the aerosol into their eyes and be advised that this may result in precipitation or worsening of narrow-angle glaucoma, mydriasis, increased intraocular pressure, acute eye pain or discomfort, temporary blurring of vision, visual halos or colored images in association with red eyes from conjunctival and corneal congestion. Patients should also be advised that should any combination of these symptoms develop, they should consult their physician immediately.

The action of Atrovent® HFA (ipratropium bromide HFA) Inhalation Aerosol should last 2-4 hours. Patients should be advised not to increase the dose or frequency of ATROVENT HFA Inhalation Aerosol without patients consulting their physician. Patients should also be advised to seek immediate medical attention if treatment with ATROVENT HFA Inhalation Aerosol becomes less effective for symptomatic relief, their symptoms become worse, and/or patients need to use the product more frequently than usual.

Patients should be advised on the use of ATROVENT HFA Inhalation Aerosol in relation to other inhaled drugs.

Patients should be reminded that ATROVENT HFA Inhalation Aerosol should be used consistently as prescribed throughout the course of therapy.

Patients should be advised that although the taste and inhalation sensation of ATROVENT HFA Inhalation Aerosol may be slightly different from that of the CFC (chlorofluorocarbon) formulation of ATROVENT Inhalation Aerosol, they are comparable in terms of safety and efficacy.

Since dizziness, accommodation disorder, mydriasis, and blurred vision may occur with use of ATROVENT, patients should be cautioned about engaging in activities requiring balance and visual acuity such as driving a car or operating appliances, machinery, etc.

Drug Interactions

ATROVENT HFA Inhalation Aerosol has been used concomitantly with other drugs, including sympathomimetic bronchodilators, methylxanthines, oral and inhaled steroids, that may be used in the treatment of chronic obstructive pulmonary disease. With the exception of albuterol, there are no formal studies fully evaluating the interaction effects of ATROVENT and these drugs with respect to effectiveness.

Anticholinergic agents: There is potential for an additive interaction with concomitantly used anticholinergic medications. Caution is therefore advised in the co-administration of ATROVENT HFA Inhalation Aerosol with other anticholinergic-containing drugs.

Carcinogenesis, Mutagenesis, Impairment of Fertility

Two-year oral carcinogenicity studies in rats and mice have revealed no carcinogenic activity at doses up to 6 mg/kg (approximately 240 and 120 times the maximum recommended daily inhalation dose in adults on a mg/m^2 basis). Results of various mutagenicity studies (Ames test, mouse dominant lethal test, mouse micronucleus test and chromosome aberration of bone marrow in Chinese hamsters) were negative.

Fertility of male or female rats at oral doses up to 50 mg/kg (approximately 2000 times the maximum recommended daily inhalation dose in adults on a mg/m^2 basis) was unaffected by ipratropium bromide administration. At an oral dose of 500 mg/kg (approximately 20,000 times the maximum recommended daily inhalation dose in adults on a mg/m^2 basis), ipratropium bromide produced a decrease in the conception rate.

Pregnancy

Teratogenic Effects: Pregnancy Category B.

Oral reproduction studies were performed at doses of 10 mg/kg/day in mice, 1,000 mg/kg in rats and 125 mg/kg/day in rabbits. These doses correspond in each species, respectively, to approximately 200, 40000, and 10000 times the maximum recommended daily inhalation dose in adults on a mg/m^2 basis. Inhalation reproduction studies were conducted in rats and rabbits at doses of 1.5 and 1.8 mg/kg (approximately 60 and 140 times the maximum recommended daily inhalation dose in adults on a mg/m^2 basis). These studies demonstrated no evidence of teratogenic effects as a result of ipratropium bromide. At oral doses 90 mg/kg and above in rats (approximately 3600 times the maximum recommended daily inhalation dose in adults on a mg/m^2 basis) embryotoxicity was observed as increased resorption. This effect is not considered relevant to human use due to the large doses at which it was observed and the difference in route of administration. There are, however, no adequate and well-controlled studies in pregnant women. Because animal reproduction studies are not always predictive of human response, Atrovent® HFA (ipratropium bromide HFA) Inhalation Aerosol should be used during pregnancy only if clearly needed.

Nursing Mothers

It is not known whether the active component, ipratropium bromide, is excreted in human milk. Because lipid-insoluble quaternary cations pass into breast milk, caution should be exercised when ATROVENT HFA Inhalation Aerosol is administered to a nursing mother.

Pediatric Use

Safety and effectiveness in the pediatric population have not been established.

Geriatric Use

In the pivotal 12-week study, both ATROVENT HFA Inhalation Aerosol and Atrovent® (ipratropium bromide) Inhalation Aerosol CFC formulations were equally effective in patients over 65 years of age and under 65 years of age.

Of the total number of subjects in clinical studies of ATROVENT HFA Inhalation Aerosol, 57% were ≥ 65 years of age. No overall differences in safety or effectiveness were observed between these subjects and younger subjects.

ADVERSE REACTIONS

The adverse reaction information concerning ATROVENT HFA Inhalation Aerosol is derived from two 12-week, double-blind, parallel group studies and one open-label, parallel group study that compared ATROVENT HFA Inhalation Aerosol, ATROVENT Inhalation Aerosol CFC, and placebo (in one study only) in 1,010 COPD patients. The following table lists the incidence of adverse events that occurred at a rate of greater than or equal to 3% in any ipratropium bromide group. Overall, the incidence and nature of the adverse events reported for ATROVENT HFA Inhalation Aerosol, ATROVENT Inhalation Aerosol CFC, and placebo were comparable.

TABLE 1 Adverse Experiences Reported in ≥ 3% of Patients in any Ipratropium Bromide Group
 | Placebo-controlled 12 week Study 244.1405 and Active-controlled 12 week Study 244.1408 |  |  | Active-controlled 1-year Study 244.2453
 | Atrovent HFA (N=243) % | Atrovent CFC (N=183) % | Placebo (N=128) % | Atrovent HFA (N=305) % | Atrovent CFC (N=151) %
Total With Any Adverse Event | 63 | 68 | 72 | 91 | 87
BODY AS A WHOLE - GENERAL DISORDERS
Back pain | 2 | 3 | 2 | 7 | 3
Headache | 6 | 9 | 8 | 7 | 5
Influenza-like symptoms | 4 | 2 | 2 | 8 | 5
CENTRAL & PERIPHERAL NERVOUS SYSTEM DISORDERS
Dizziness | 3 | 3 | 2 | 3 | 1
GASTROINTESTINAL SYSTEM DISORDERS
Dyspepsia | 1 | 3 | 1 | 5 | 3
Mouth dry | 4 | 2 | 2 | 2 | 3
Nausea | 4 | 1 | 2 | 4 | 4
RESPIRATORY SYSTEM DISORDERS
Bronchitis | 10 | 11 | 6 | 23 | 19
COPD exacerbation | 8 | 14 | 13 | 23 | 23
Coughing | 3 | 4 | 6 | 5 | 5
Dyspnea | 8 | 8 | 4 | 7 | 4
Rhinitis | 4 | 2 | 4 | 6 | 2
Sinusitis | 1 | 4 | 3 | 11 | 14
Upper respiratory tract infection | 9 | 10 | 16 | 34 | 34
URINARY SYSTEM DISORDERS
Urinary tract infection | 2 | 3 | 1 | 10 | 8

In the one open label controlled study in 456 COPD patients, the overall incidence of adverse events was also similar between Atrovent® HFA (ipratropium bromide HFA) Inhalation Aerosol and Atrovent® (ipratropium bromide) Inhalation Aerosol CFC formulations.

Overall, in the above mentioned studies, 9.3% of the patients taking 42 mcg ATROVENT HFA Inhalation Aerosol and 8.7% of the patients taking 42 mcg ATROVENT Inhalation Aerosol CFC reported at least one adverse event that was considered by the investigator to be related to the study drug. The most common drug-related adverse events were dry mouth (1.6% of ATROVENT HFA Inhalation Aerosol and 0.9% of ATROVENT Inhalation Aerosol CFC patients), and taste perversion (bitter taste) (0.9% of ATROVENT HFA Inhalation Aerosol and 0.3% of ATROVENT Inhalation Aerosol CFC patients).

As an anticholinergic drug, cases of precipitation or worsening of narrow-angle glaucoma, glaucoma, halo vision, conjunctival hyperaemia, corneal edema, mydriasis, acute eye pain, dry throat, hypotension, palpitations, urinary retention, tachycardia, constipation, bronchospasm, including paradoxical bronchospasm have been reported. Additional cases identified for ATROVENT seen in clinical trials include throat irritation, stomatitis, mouth edema, and vision blurred.

Allergic-type reactions such as skin rash, pruritus, angioedema including that of tongue, lips and face, urticaria (including giant urticaria), laryngospasm and anaphylactic reactions have been reported (see CONTRAINDICATIONS).

Post-Marketing Experience

In a 5-year placebo-controlled trial, hospitalizations for supraventricular tachycardia and/or atrial fibrillation occurred with an incidence rate of 0.5% in COPD patients receiving ATROVENT Inhalation Aerosol CFC.

Allergic-type reactions such as skin rash, angioedema including that of tongue, lips and face, urticaria (including giant urticaria), laryngospasm and anaphylactic reactions have been reported, with positive rechallenge in some cases.

Additionally, urinary retention, mydriasis, gastrointestinal distress (diarrhea, nausea, vomiting), and bronchospasm, including paradoxical bronchospasm, hypersensitivity reactions, intraocular pressure increased, accommodation disorder, heart rate increased, pharyngeal edema, and gastrointestinal motility disorders have been reported during the post-marketing period with use of ATROVENT.

OVERDOSAGE

Acute overdose by inhalation is unlikely since ipratropium bromide is not well absorbed systemically after inhalation or oral administration. Oral median lethal doses of ipratropium bromide were greater than 1001 mg/kg in mice (approximately 20,000 times the maximum recommended daily inhalation dose in adults on a mg/m^2 basis); 1,663 mg/kg in rats (approximately 66,000 times the maximum recommended daily inhalation dose in adults on a mg/m^2 basis); and 400 mg/kg in dogs (approximately 53,000 times the maximum recommended daily inhalation dose in adults on a mg/m^2 basis).

DOSAGE AND ADMINISTRATION

Patients should be instructed on the proper use of their inhaler (see Patient's Instructions for Use).

Patients should be advised that although Atrovent® HFA (ipratropium bromide HFA) Inhalation Aerosol may have a slightly different taste and inhalation sensation than that of an inhaler containing Atrovent® (ipratropium bromide) Inhalation Aerosol CFC, they are comparable in terms of the safety and efficacy.

ATROVENT HFA Inhalation Aerosol is a solution aerosol that does not require shaking. However, as with any other metered dose inhaler, some coordination is required between actuating the canister and inhaling the medication.

Patients should "prime" or actuate ATROVENT HFA Inhalation Aerosol before using for the first time by releasing 2 test sprays into the air away from the face. In cases where the inhaler has not been used for more than 3 days, prime the inhaler again by releasing 2 test sprays into the air away from the face. Patients should avoid spraying ATROVENT HFA Inhalation Aerosol into their eyes.

The usual starting dose of ATROVENT HFA Inhalation Aerosol is two inhalations four times a day. Patients may take additional inhalations as required; however, the total number of inhalations should not exceed 12 in 24 hours. Each actuation of ATROVENT HFA Inhalation Aerosol delivers 17 mcg of ipratropium bromide from the mouthpiece.

HOW SUPPLIED

ATROVENT HFA Inhalation Aerosol is supplied in a 12.9 g pressurized stainless steel canister as a metered-dose inhaler with a white mouthpiece that has a clear, colorless sleeve and a green protective cap (NDC 54868-5511-0).

The ATROVENT HFA Inhalation Aerosol canister is to be used only with the accompanying ATROVENT HFA Inhalation Aerosol mouthpiece. This mouthpiece should not be used with other aerosol medications. Similarly, the canister should not be used with other mouthpieces. Each actuation of ATROVENT HFA Inhalation Aerosol delivers 21 mcg of ipratropium bromide from the valve and 17 mcg from the mouthpiece. Each 12.9 gram canister provides sufficient medication for 200 actuations. The canister should be discarded after the labeled number of actuations has been used. The amount of medication in each actuation cannot be assured after this point, even though the canister is not completely empty.

STORAGE AND HANDLING

Store at 25°C (77°F); excursions permitted to 15°-30°C (59°-86°F) [see USP Controlled Room Temperature]. For optimal results, the canister should be at room temperature before use.

Address medical inquiries to: http://us.boehringer-ingelheim.com, (800) 542-6257 or (800) 459-9906 TTY.

Patients should be reminded to read and follow the accompanying “Patient's Instructions for Use”, which should be dispensed with the product.

Contents Under Pressure: Do not puncture. Do not use or store near heat or open flame. Exposure to temperatures above 120°F may cause bursting. Never throw the inhaler into a fire or incinerator.

Warning: Keep out of children's reach. Avoid spraying in eyes.

Distributed by:
Boehringer Ingelheim Pharmaceuticals, Inc.
Ridgefield, CT 06877 USA

Licensed from:
Boehringer Ingelheim International GmbH

Copyright 2010 Boehringer Ingelheim International GmbH
ALL RIGHTS RESERVED

Rev: July 2010

IT1902GG1710
10003001/06

Relabeling of "Additional Barcode Label" by:
Physicians Total Care, Inc.
Tulsa, OK 74146

Patient's Instructions for Use

Atrovent® HFA
(ipratropium bromide HFA)
Inhalation Aerosol

Read complete instructions carefully before using.

Important Points to Remember About Using ATROVENT HFA Inhalation Aerosol

Although ATROVENT HFA Inhalation Aerosol may taste and feel different
when breathed in compared to your Atrovent® (ipratropium
bromide) Inhalation Aerosol CFC inhaler, they contain the same
medicine.

You do not have to shake the ATROVENT HFA Inhalation Aerosol canister
before using it.

ATROVENT HFA Inhalation Aerosol should be "primed" two times before
taking the first dose from a new inhaler or when the inhaler has not been used for
more than three days. To prime, push the canister against the mouthpiece (see
Figure 1), allowing the medicine to spray into the air. Avoid spraying the
medicine into your eyes while priming ATROVENT HFA Inhalation
Aerosol.

Ask your doctor how to use other inhaled medicines with ATROVENT HFA Inhalation Aerosol.

Use ATROVENT HFA Inhalation Aerosol exactly as prescribed by your doctor. Do not change your dose or how often you use ATROVENT HFA Inhalation Aerosol without talking with your doctor. Talk to your doctor if you have questions about your medical condition or your treatment.

Instructions

1. Insert the metal canister into the clear end of the mouthpiece (see Figure 1). Make sure the canister is fully and firmly inserted into the mouthpiece. The ATROVENT HFA Inhalation Aerosol canister is for use only with the ATROVENT HFA Inhalation Aerosol mouthpiece. Do not use the ATROVENT HFA Inhalation Aerosol canister with other mouthpieces. This mouthpiece should not be used with other inhaled medicines.
  Figure 1
2. Remove the green protective dust cap. If the cap is not on the mouthpiece, make sure there is nothing in the mouthpiece before use. For best results, the canister should be at room temperature before use.
3. Breathe out (exhale) deeply through your mouth. Hold the canister upright as shown in Figure 2, between your thumb and first 2 fingers. Put the mouthpiece in your mouth and close your lips. Keep your eyes closed so that no medicine will be sprayed into your eyes. Atrovent® HFA (ipratropium bromide HFA) Inhalation Aerosol can cause blurry vision, narrow-angle glaucoma or worsening of this condition or eye pain if the medicine is sprayed into your eyes.
  Figure 2
4. Breathe in (inhale) slowly through your mouth and at the same time firmly press once on the canister against the mouthpiece as shown in Figure 3. Keep breathing in deeply.
  Figure 3
5. Hold your breath for ten seconds and then remove the mouthpiece from your mouth and breathe out slowly, as in Figure 4. Wait at least 15 seconds and repeat steps 3 to 5 again.
  Figure 4
6. Replace the green protective dust cap after use.
7. Keep the mouthpiece clean. It is very important to keep the mouthpiece clean. At least once a week, wash the mouthpiece, shake it to remove excess water and let it air dry all the way (see the instructions below).
  Mouthpiece Cleaning Instructions:
  Step A. Remove and set aside the canister and dust cap from the mouthpiece (see Figure 1).
  Step B. Wash the mouthpiece through the top and bottom with warm running water for at least 30 seconds (see Figure 5). Do not use anything other than water to wash the mouthpiece.
  Figure 5
  Step C. Dry the mouthpiece by shaking off the excess water and allow it to air-dry all the way.
  Step D. When the mouthpiece is dry, replace the canister. Make sure the canister is fully and firmly inserted into the mouthpiece.
  Step E. Replace the green protective dust cap.
  If the mouthpiece becomes blocked, and little or no medicine comes out of the mouthpiece, wash the mouthpiece as described in Steps A to E under the “Mouthpiece Cleaning Instructions”.
8. Keep track of the number of sprays used. Discard the canister after 200 sprays. Even though the canister is not empty, you cannot be sure of the amount of medicine in each spray after 200 sprays.

This product does not contain any chlorofluorocarbon (CFC) propellants.

The contents of Atrovent® HFA (ipratropium bromide HFA) Inhalation Aerosol are under pressure. Do not puncture the canister. Do not use or store near heat or open flame. Exposure to temperatures above 120°F may cause bursting. Never throw the container into a fire or incinerator.

Keep ATROVENT HFA Inhalation Aerosol and all medicines out of the reach of children.

Avoid spraying into eyes.

Address medical inquiries to: http://us.boehringer-ingelheim.com, (800) 542-6257 or (800) 459-9906 TTY.

Store at 25°C (77°F); excursions permitted to 15°-30°C (59°-86°F). For best results, store the canister at room temperature before use.

Distributed by:
Boehringer Ingelheim Pharmaceuticals, Inc.
Ridgefield, CT 06877 USA

Licensed from:
Boehringer Ingelheim International GmbH

Distributed by:
Boehringer Ingelheim Pharmaceuticals, Inc.
Ridgefield, CT 06877 USA

Licensed from:
Boehringer Ingelheim International GmbH

Copyright 2010 Boehringer Ingelheim International GmbH
ALL RIGHTS RESERVED

Rev: July 2010

IT1902GG1710
10003001/06

PACKAGE LABEL

Atrovent® HFA
Inhalation Aerosol
12.9 grams (200 metered actuations)